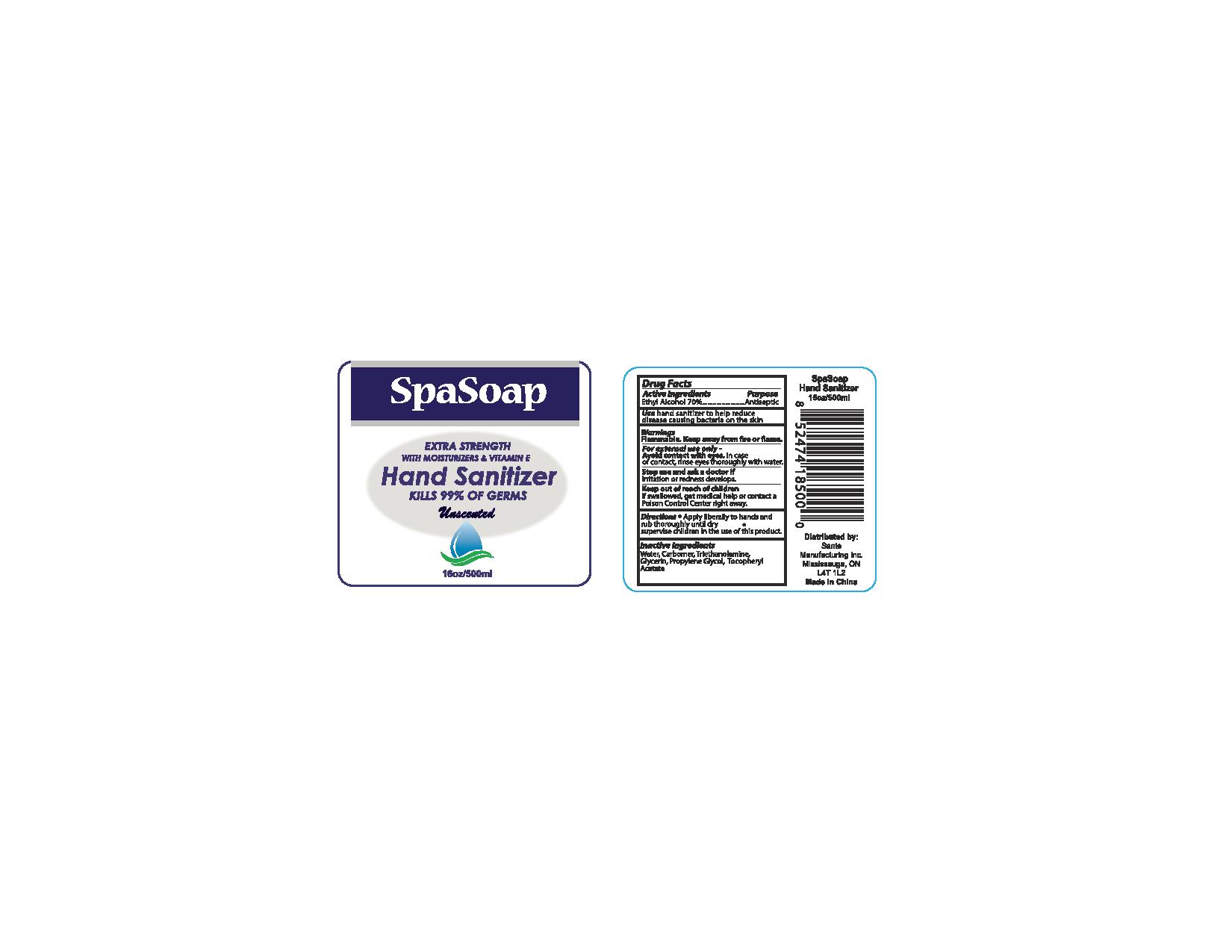 DRUG LABEL: Unscented
NDC: 71020-013 | Form: LIQUID
Manufacturer: Sante Manufacturing Inc
Category: otc | Type: HUMAN OTC DRUG LABEL
Date: 20170311

ACTIVE INGREDIENTS: ALCOHOL 700 mL/1000 mL
INACTIVE INGREDIENTS: .ALPHA.-TOCOPHEROL ACETATE; WATER; CARBOMER 940; GLYCERIN

Active Ingredients - Ethyl Alcohol 70%

Purpose - Antiseptic

INDICATIONS AND USAGE

Use hand sanitizer to help reduce disease causing bacteria on the skin

Warnings

Flammable

OTHER SAFETY INFORMATION

Keep away from fire or flame

WHEN USING

Avoid contact with eyes. In case of contact, rinse eyes thoroughly with water

Stop use and ask a doctor if irritation or rdeness develops

Keep out of reach of children

if swallowed, get medical help or contact a Poison Control Center right away

Directions

- Apply liberally to hands and rub thoroughly until dry
- supervise children in the use of this product

Inactive Ingredients

Water, Carbomer, Triethanolamine, Glycerin, Propylene Glycol, Tocopheryl Acetate

PACKAGE LABEL

Spasoap

Extra Strength with moisturizers & Vitamin E

Hand Sanitizer

Kills 99% of germs

Unscented

16oz / 500ml